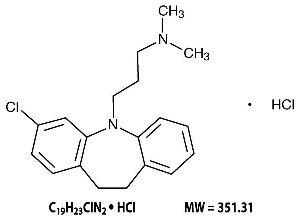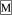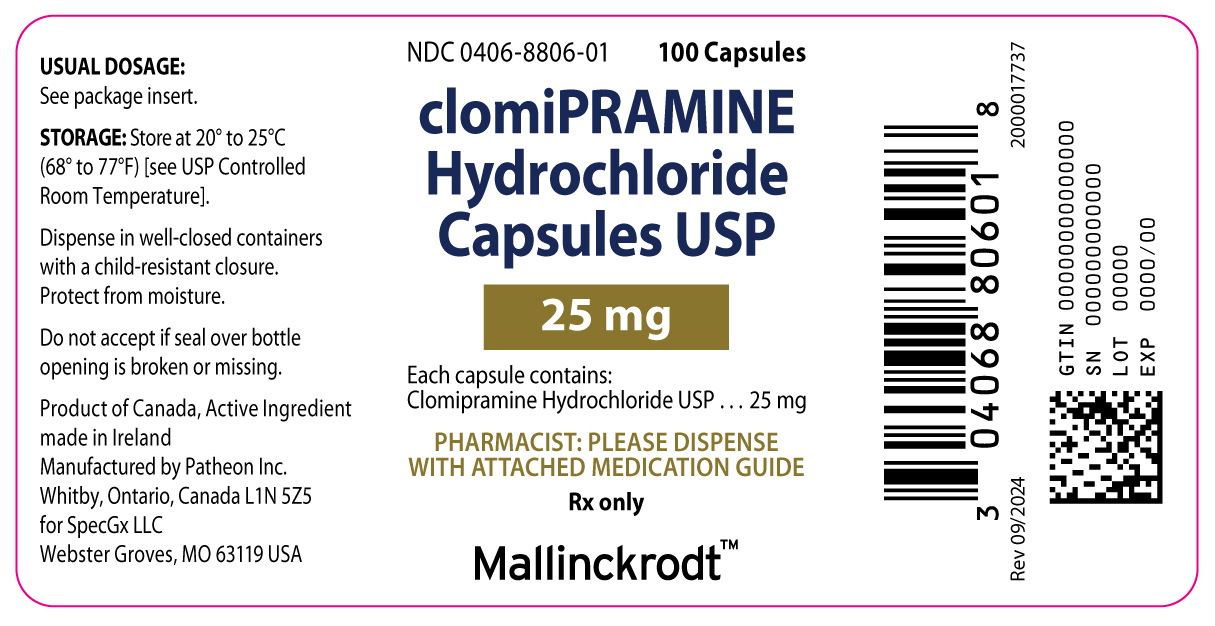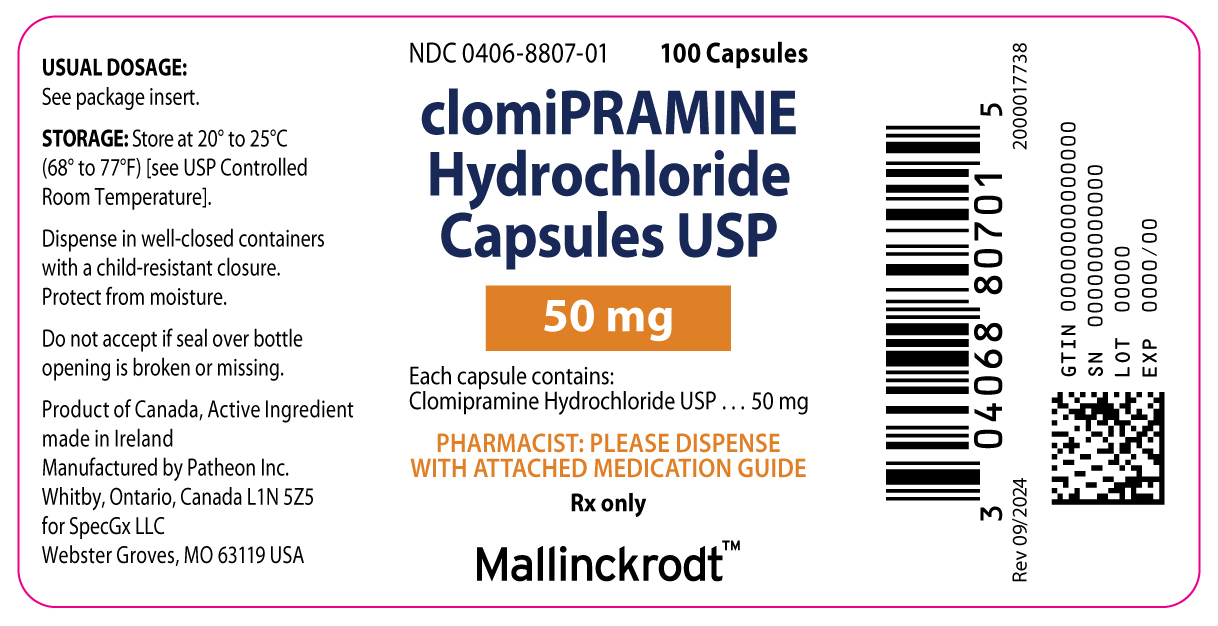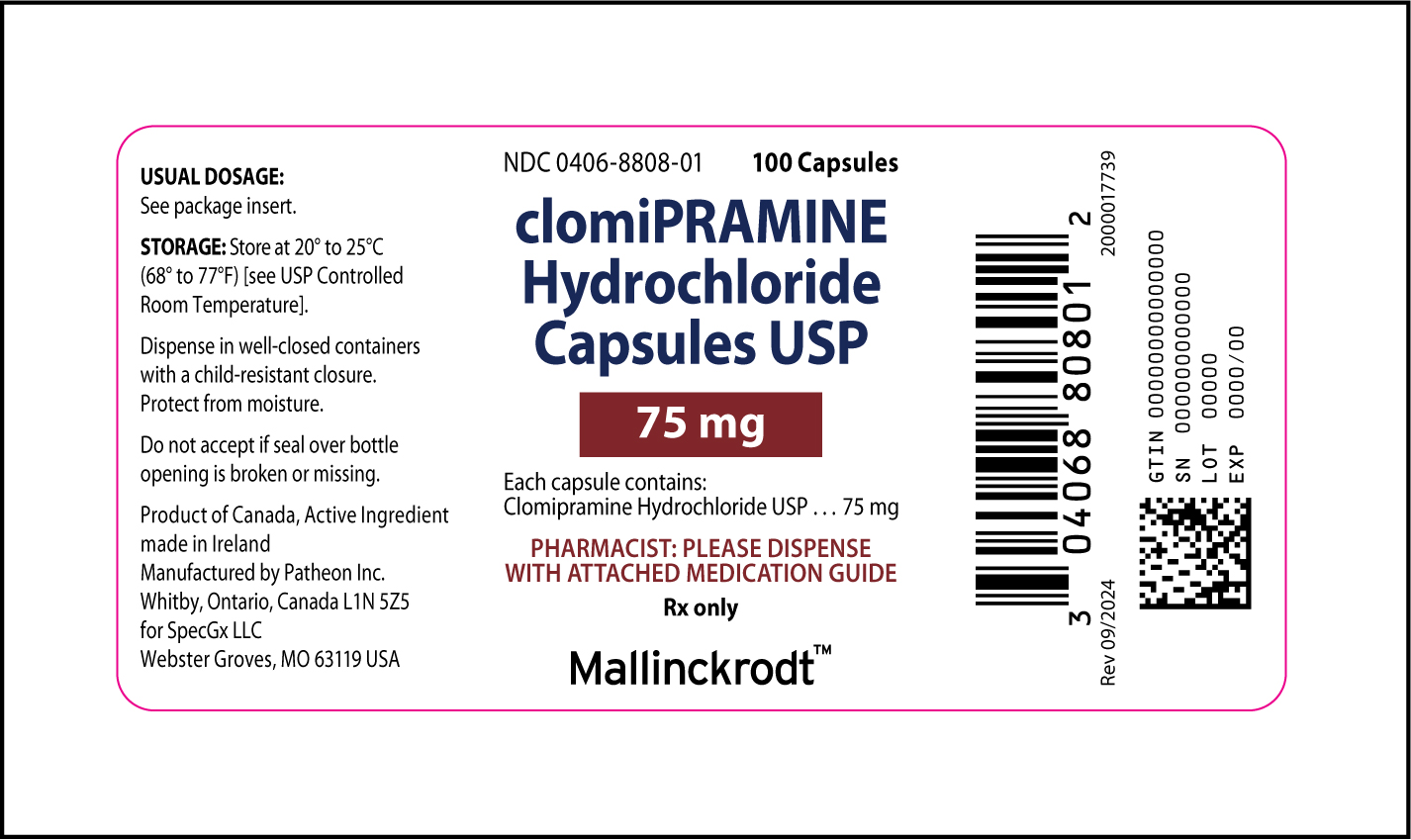 DRUG LABEL: CLOMIPRAMINE HYDROCHLORIDE
NDC: 0406-8806 | Form: CAPSULE
Manufacturer: SpecGx LLC
Category: prescription | Type: HUMAN PRESCRIPTION DRUG LABEL
Date: 20241126

ACTIVE INGREDIENTS: CLOMIPRAMINE HYDROCHLORIDE 25 mg/1 1
INACTIVE INGREDIENTS: D&C RED NO. 33; D&C YELLOW NO. 10; FD&C YELLOW NO. 6; GELATIN, UNSPECIFIED; MAGNESIUM STEARATE; METHYLPARABEN; PROPYLPARABEN; STARCH, CORN; TITANIUM DIOXIDE

Clomipramine Hydrochloride Capsules USP
(25 mg, 50 mg, and 75 mg)
Rx only

BOXED WARNING

Suicidality and Antidepressant Drugs

Antidepressants increased the risk compared to placebo of suicidal thinking and behavior (suicidality) in children, adolescents, and young adults in short-term studies of major depressive disorder (MDD) and other psychiatric disorders. Anyone considering the use of clomipramine hydrochloride or any other antidepressant in a child, adolescent, or young adult must balance this risk with the clinical need. Short-term studies did not show an increase in the risk of suicidality with antidepressants compared to placebo in adults beyond age 24; there was a reduction in risk with antidepressants compared to placebo in adults aged 65 and older. Depression and certain other psychiatric disorders are themselves associated with increases in the risk of suicide. Patients of all ages who are started on antidepressant therapy should be monitored appropriately and observed closely for clinical worsening, suicidality, or unusual changes in behavior. Families and caregivers should be advised of the need for close observation and communication with the prescriber. Clomipramine hydrochloride is not approved for use in pediatric patients except for patients with obsessive compulsive disorder (OCD) (see WARNINGS, Clinical Worsening and Suicide Risk; PRECAUTIONS, Information for Patients; and PRECAUTIONS, Pediatric Use).

DESCRIPTION

Clomipramine Hydrochloride Capsules USP are an antiobsessional drug that belongs to the class (dibenzazepine) of pharmacologic agents known as tricyclic antidepressants. Clomipramine hydrochloride capsules are available as capsules of 25, 50, and 75 mg for oral administration.

Clomipramine hydrochloride USP is 3-chloro-5-[3-(dimethylamino)propyl]-10,11-dihydro-5H-dibenz[b,f]azepine monohydrochloride, and its structural formula is:

Clomipramine hydrochloride USP is a white to off-white crystalline powder. It is freely soluble in water, in methanol, and in methylene chloride, and insoluble in ethyl ether and in hexane.

Inactive Ingredients. D&C Red No. 33 (25 mg capsules only), D&C Yellow No. 10, FD&C Blue No. 1 (50 mg capsules only), FD&C Yellow No. 6, gelatin, magnesium stearate, methylparaben, propylparaben, starch (corn), and titanium dioxide.

CLINICAL PHARMACOLOGY

Pharmacodynamics

Clomipramine (CMI) is presumed to influence obsessive and compulsive behaviors through its effects on serotonergic neuronal transmission. The actual neurochemical mechanism is unknown, but CMI’s capacity to inhibit the reuptake of serotonin (5-HT) is thought to be important.

Pharmacokinetics

Absorption/Bioavailability – CMI from clomipramine hydrochloride capsules is as bioavailable as CMI from a solution. The bioavailability of CMI from capsules is not significantly affected by food.

In a dose proportionality study involving multiple CMI doses, steady-state plasma concentrations (Css) and area-under-plasma-concentration-time curves (AUC) of CMI and CMI’s major active metabolite, desmethylclomipramine (DMI), were not proportional to dose over the ranges evaluated, i.e., between 25 to 100 mg/day and between 25 to 150 mg/day, although Css and AUC are approximately linearly related to dose between 100 to 150 mg/day. The relationship between dose and CMI/DMI concentrations at higher daily doses has not been systematically assessed, but if there is significant dose dependency at doses above 150 mg/day, there is the potential for dramatically higher Css and AUC even for patients dosed within the recommended range. This may pose a potential risk to some patients (see WARNINGS and PRECAUTIONS, Drug Interactions).

After a single 50 mg oral dose, maximum plasma concentrations of CMI occur within 2 to 6 hours (mean, 4.7 hr) and range from 56 ng/mL to 154 ng/mL (mean, 92 ng/mL). After multiple daily doses of 150 mg of clomipramine hydrochloride capsules, steady-state maximum plasma concentrations range from 94 ng/mL to 339 ng/mL (mean, 218 ng/mL) for CMI and from 134 ng/mL to 532 ng/mL (mean, 274 ng/mL) for DMI. Additional information from a rising dose study of doses up to 250 mg suggests that DMI may exhibit nonlinear pharmacokinetics over the usual dosing range. At a dose of clomipramine hydrochloride capsules 200 mg, subjects who had a single blood sample taken approximately 9 to 22 hours, (median 16 hours), after the dose had plasma concentrations of up to 605 ng/mL for CMI, 781 ng/mL for DMI, and 1386 ng/mL for both.

Distribution – CMI distributes into cerebrospinal fluid (CSF) and brain and into breast milk. DMI also distributes into CSF, with a mean CSF/plasma ratio of 2.6. The protein binding of CMI is approximately 97%, principally to albumin, and is independent of CMI concentration. The interaction between CMI and other highly protein-bound drugs has not been fully evaluated, but may be important (see PRECAUTIONS, Drug Interactions).

Metabolism – CMI is extensively biotransformed to DMI and other metabolites and their glucuronide conjugates. DMI is pharmacologically active, but its effects on OCD behaviors are unknown. These metabolites are excreted in urine and feces, following biliary elimination. After a 25 mg radiolabeled dose of CMI in two subjects, 60% and 51%, respectively, of the dose were recovered in the urine and 32% and 24%, respectively, in feces. In the same study, the combined urinary recoveries of CMI and DMI were only about 0.8% to 1.3% of the dose administered. CMI does not induce drug-metabolizing enzymes, as measured by antipyrine half-life.

Elimination – Evidence that the Css and AUC for CMI and DMI may increase disproportionately with increasing oral doses suggests that the metabolism of CMI and DMI may be capacity limited. This fact must be considered in assessing the estimates of the pharmacokinetic parameters presented below, as these were obtained in individuals exposed to doses of 150 mg. If the pharmacokinetics of CMI and DMI are nonlinear at doses above 150 mg, their elimination half-lives may be considerably lengthened at doses near the upper end of the recommended dosing range (i.e., 200 mg/day to 250 mg/day). Consequently, CMI and DMI may accumulate, and this accumulation may increase the incidence of any dose- or plasma-concentration-dependent adverse reactions, in particular seizures (see WARNINGS).

After a 150 mg dose, the half-life of CMI ranges from 19 hours to 37 hours (mean, 32 hr) and that of DMI ranges from 54 hours to 77 hours (mean, 69 hr). Steady-state levels after multiple dosing are typically reached within 7 to 14 days for CMI. Plasma concentrations of the metabolite exceed the parent drug on multiple dosing. After multiple dosing with 150 mg/day, the accumulation factor for CMI is approximately 2.5 and for DMI is 4.6. Importantly, it may take two weeks or longer to achieve this extent of accumulation at constant dosing because of the relatively long elimination half-lives of CMI and DMI (see DOSAGE AND ADMINISTRATION). The effects of hepatic and renal impairment on the disposition of clomipramine hydrochloride capsules have not been determined.

Interactions – Co-administration of haloperidol with CMI increases plasma concentrations of CMI. Co-administration of CMI with phenobarbital increases plasma concentrations of phenobarbital (see PRECAUTIONS, Drug Interactions). Younger subjects (18 to 40 years of age) tolerated CMI better and had significantly lower steady-state plasma concentrations, compared with subjects over 65 years of age. Children under 15 years of age had significantly lower plasma concentration/dose ratios, compared with adults. Plasma concentrations of CMI were significantly lower in smokers than in nonsmokers.

INDICATIONS AND USAGE

Clomipramine Hydrochloride Capsules USP are indicated for the treatment of obsessions and compulsions in patients with Obsessive-Compulsive Disorder (OCD). The obsessions or compulsions must cause marked distress, be time-consuming, or significantly interfere with social or occupational functioning, in order to meet the DSM-III-R (circa 1989) diagnosis of OCD.

Obsessions are recurrent, persistent ideas, thoughts, images, or impulses that are ego-dystonic. Compulsions are repetitive, purposeful, and intentional behaviors performed in response to an obsession or in a stereotyped fashion, and are recognized by the person as excessive or unreasonable.

The effectiveness of clomipramine hydrochloride capsules for the treatment of OCD was demonstrated in multicenter, placebo-controlled, parallel-group studies, including two 10-week studies in adults and one 8-week study in children and adolescents 10 to 17 years of age. Patients in all studies had moderate-to-severe OCD (DSM-III), with mean baseline ratings on the Yale-Brown Obsessive Compulsive Scale (YBOCS) ranging from 26 to 28 and a mean baseline rating of 10 on the NIMH Clinical Global Obsessive Compulsive Scale (NIMH-OC). Patients taking CMI experienced a mean reduction of approximately 10 on the YBOCS, representing an average improvement on this scale of 35% to 42% among adults and 37% among children and adolescents. CMI-treated patients experienced a 3.5 unit decrement on the NIMH-OC. Patients on placebo showed no important clinical response on either scale. The maximum dose was 250 mg/day for most adults and 3 mg/kg/day (up to 200 mg) for all children and adolescents.

The effectiveness of clomipramine hydrochloride capsules for long-term use (i.e., for more than 10 weeks) has not been systematically evaluated in placebo-controlled trials. The physician who elects to use clomipramine hydrochloride capsules for extended periods should periodically reevaluate the long-term usefulness of the drug for the individual patient (see DOSAGE AND ADMINISTRATION).

CONTRAINDICATIONS

Clomipramine hydrochloride capsules are contraindicated in patients with a history of hypersensitivity to clomipramine hydrochloride capsules or other tricyclic antidepressants.

Monoamine Oxidase Inhibitors (MAOIs)

The use of MAOIs intended to treat psychiatric disorders with clomipramine hydrochloride capsules or within 14 days of stopping treatment with clomipramine hydrochloride capsules is contraindicated because of an increased risk of serotonin syndrome. The use of clomipramine hydrochloride capsules within 14 days of stopping an MAOI intended to treat psychiatric disorders is also contraindicated (see WARNINGS and DOSAGE AND ADMINISTRATION).

Starting clomipramine hydrochloride capsules in a patient who is being treated with linezolid or intravenous methylene blue is also contraindicated because of an increased risk of serotonin syndrome (see WARNINGS and DOSAGE AND ADMINISTRATION).

Myocardial Infarction

Clomipramine hydrochloride capsules are contraindicated during the acute recovery period after a myocardial infarction.

WARNINGS

Clinical Worsening and Suicide Risk

Patients with major depressive disorder (MDD), both adult and pediatric, may experience worsening of their depression and/or the emergence of suicidal ideation and behavior (suicidality) or unusual changes in behavior, whether or not they are taking antidepressant medications, and this risk may persist until significant remission occurs. Suicide is a known risk of depression and certain other psychiatric disorders, and these disorders themselves are the strongest predictors of suicide. There has been a long-standing concern, however, that antidepressants may have a role in inducing worsening of depression and the emergence of suicidality in certain patients during the early phases of treatment. Pooled analyses of short-term placebo-controlled trials of antidepressant drugs (SSRIs and others) showed that these drugs increase the risk of suicidal thinking and behavior (suicidality) in children, adolescents, and young adults (ages 18 to 24) with major depressive disorder (MDD) and other psychiatric disorders. Short-term studies did not show an increase in the risk of suicidality with antidepressants compared to placebo in adults beyond age 24; there was a reduction with antidepressants compared to placebo in adults aged 65 and older.

The pooled analyses of placebo-controlled trials in children and adolescents with MDD, obsessive compulsive disorder (OCD), or other psychiatric disorders included a total of 24 short-term trials of 9 antidepressant drugs in over 4400 patients. The pooled analyses of placebo-controlled trials in adults with MDD or other psychiatric disorders included a total of 295 short-term trials (median duration of 2 months) of 11 antidepressant drugs in over 77,000 patients. There was considerable variation in risk of suicidality among drugs, but a tendency toward an increase in the younger patients for almost all drugs studied. There were differences in absolute risk of suicidality across the different indications, with the highest incidence in MDD. The risk differences (drug vs. placebo), however, were relatively stable within age strata and across indications. These risk differences (drug-placebo difference in the number of cases of suicidality per 1000 patients treated) are provided in Table 1.

Table 1
Age Range | Drug-Placebo Difference in; Number of Cases of Suicidality; per 1000 Patients Treated
Increases Compared to Placebo
<18 | 14 additional cases
18-24 | 5 additional cases
Decreases Compared to Placebo
25-64 | 1 fewer case
≥65 | 6 fewer cases

No suicides occurred in any of the pediatric trials. There were suicides in the adult trials, but the number was not sufficient to reach any conclusion about drug effect on suicide.

It is unknown whether the suicidality risk extends to longer-term use, i.e., beyond several months. However, there is substantial evidence from placebo-controlled maintenance trials in adults with depression that the use of antidepressants can delay the recurrence of depression.

All patients being treated with antidepressants for any indication should be monitored appropriately and observed closely for clinical worsening, suicidality, and unusual changes in behavior, especially during the initial few months of a course of drug therapy, or at times of dose changes, either increases or decreases.

The following symptoms, anxiety, agitation, panic attacks, insomnia, irritability, hostility, aggressiveness, impulsivity, akathisia (psychomotor restlessness), hypomania, and mania, have been reported in adult and pediatric patients being treated with antidepressants for major depressive disorder as well as for other indications, both psychiatric and nonpsychiatric. Although a causal link between the emergence of such symptoms and either the worsening of depression and/or the emergence of suicidal impulses has not been established, there is concern that such symptoms may represent precursors to emerging suicidality.

Consideration should be given to changing the therapeutic regimen, including possibly discontinuing the medication, in patients whose depression is persistently worse, or who are experiencing emergent suicidality or symptoms that might be precursors to worsening depression or suicidality, especially if these symptoms are severe, abrupt in onset, or were not part of the patient’s presenting symptoms.

Families and caregivers of patients being treated with antidepressants for major depressive disorder or other indications, both psychiatric and nonpsychiatric, should be alerted about the need to monitor patients for the emergence of agitation, irritability, unusual changes in behavior, and the other symptoms described above, as well as the emergence of suicidality, and to report such symptoms immediately to healthcare providers. Such monitoring should include daily observation by families and caregivers. Prescriptions for clomipramine hydrochloride should be written for the smallest quantity of capsules consistent with good patient management, in order to reduce the risk of overdose.

Screening Patients for Bipolar Disorder – A major depressive episode may be the initial presentation of bipolar disorder. It is generally believed (though not established in controlled trials) that treating such an episode with an antidepressant alone may increase the likelihood of precipitation of a mixed/manic episode in patients at risk for bipolar disorder. Whether any of the symptoms described above represent such a conversion is unknown. However, prior to initiating treatment with an antidepressant, patients with depressive symptoms should be adequately screened to determine if they are at risk for bipolar disorder; such screening should include a detailed psychiatric history, including a family history of suicide, bipolar disorder, and depression. It should be noted that clomipramine hydrochloride is not approved for use in treating bipolar depression.

Serotonin Syndrome

The development of a potentially life-threatening serotonin syndrome has been reported with SNRIs and SSRIs, including clomipramine hydrochloride capsules, alone but particularly with concomitant use of other serotonergic drugs (including triptans, tricyclic antidepressants, fentanyl, lithium, tramadol, tryptophan, buspirone, and St. John's Wort) and with drugs that impair metabolism of serotonin (in particular, MAOIs, both those intended to treat psychiatric disorders and also others, such as linezolid and intravenous methylene blue).

Serotonin syndrome symptoms may include mental status changes (e.g., agitation, hallucinations, delirium, and coma), autonomic instability (e.g., tachycardia, labile blood pressure, dizziness, diaphoresis, flushing, hyperthermia), neuromuscular changes (e.g., tremor, rigidity, myoclonus, hyperreflexia, incoordination), seizures, and/or gastrointestinal symptoms (e.g., nausea, vomiting, diarrhea). Patients should be monitored for the emergence of serotonin syndrome.

The concomitant use of clomipramine hydrochloride capsules with MAOIs intended to treat psychiatric disorders is contraindicated. Clomipramine hydrochloride capsules should also not be started in a patient who is being treated with MAOIs such as linezolid or intravenous methylene blue. All reports with methylene blue that provided information on the route of administration involved intravenous administration in the dose range of 1 mg/kg to 8 mg/kg. No reports involved the administration of methylene blue by other routes (such as oral tablets or local tissue injection) or at lower doses. There may be circumstances when it is necessary to initiate treatment with an MAOI such as linezolid or intravenous methylene blue in a patient taking clomipramine hydrochloride capsules. Clomipramine hydrochloride capsules should be discontinued before initiating treatment with the MAOI (see CONTRAINDICATIONS and DOSAGE AND ADMINISTRATION).

If concomitant use of clomipramine hydrochloride capsules with other serotonergic drugs, including triptans, tricyclic antidepressants, fentanyl, lithium, tramadol, buspirone, tryptophan, and St. John’s Wort is clinically warranted, patients should be made aware of a potential increased risk for serotonin syndrome, particularly during treatment initiation and dose increases.

Treatment with clomipramine hydrochloride capsules and any concomitant serotonergic agents should be discontinued immediately if the above events occur and supportive symptomatic treatment should be initiated.

Angle-Closure Glaucoma

The pupillary dilation that occurs following use of many antidepressant drugs including clomipramine hydrochloride capsules may trigger an angle closure attack in a patient with anatomically narrow angles who does not have a patent iridectomy.

Seizures

During premarket evaluation, seizure was identified as the most significant risk of clomipramine hydrochloride capsules use.

The observed cumulative incidence of seizures among patients exposed to clomipramine hydrochloride capsules at doses up to 300 mg/day was 0.64% at 90 days, 1.12% at 180 days, and 1.45% at 365 days. The cumulative rates correct the crude rate of 0.7% (25 of 3519 patients) for the variable duration of exposure in clinical trials.

Although dose appears to be a predictor of seizure, there is a confounding of dose and duration of exposure, making it difficult to assess independently the effect of either factor alone. The ability to predict the occurrence of seizures in subjects exposed to doses of CMI greater than 250 mg is limited, given that the plasma concentration of CMI may be dose-dependent and may vary among subjects given the same dose. Nevertheless, prescribers are advised to limit the daily dose to a maximum of 250 mg in adults and 3 mg/kg (or 200 mg) in children and adolescents (see DOSAGE AND ADMINISTRATION).

Caution should be used in administering clomipramine hydrochloride capsules to patients with a history of seizures or other predisposing factors, e.g., brain damage of varying etiology, alcoholism, and concomitant use with other drugs that lower the seizure threshold.

Rare reports of fatalities in association with seizures have been reported by foreign postmarketing surveillance, but not in U.S. clinical trials. In some of these cases, clomipramine hydrochloride capsules have been administered with other epileptogenic agents; in others, the patients involved had possibly predisposing medical conditions. Thus a causal association between clomipramine hydrochloride capsules treatment and these fatalities has not been established.

Physicians should discuss with patients the risk of taking clomipramine hydrochloride capsules while engaging in activities in which sudden loss of consciousness could result in serious injury to the patient or others, e.g., the operation of complex machinery, driving, swimming, climbing.

DRESS

Rare cases of drug rash with eosinophilia and systemic symptoms (DRESS) have been reported with the use of clomipramine. In the event of severe acute reactions such as DRESS, discontinue clomipramine therapy immediately and institute appropriate treatment.

PRECAUTIONS

General

Suicide – Since depression is a commonly associated feature of OCD, the risk of suicide must be considered. Prescriptions for clomipramine hydrochloride capsules should be written for the smallest quantity of capsules consistent with good patient management, in order to reduce the risk of overdose.

Cardiovascular Effects – Modest orthostatic decreases in blood pressure and modest tachycardia were each seen in approximately 20% of patients taking clomipramine hydrochloride capsules in clinical trials; but patients were frequently asymptomatic. Among approximately 1400 patients treated with CMI in the premarketing experience who had ECGs, 1.5% developed abnormalities during treatment, compared with 3.1% of patients receiving active control drugs and 0.7% of patients receiving placebo. The most common ECG changes were PVCs, ST-T wave changes, and intraventricular conduction abnormalities. These changes were rarely associated with significant clinical symptoms. Nevertheless, caution is necessary in treating patients with known cardiovascular disease, and gradual dose titration is recommended.

Psychosis, Confusion, and Other Neuropsychiatric Phenomena – Patients treated with clomipramine hydrochloride capsules have been reported to show a variety of neuropsychiatric signs and symptoms including delusions, hallucinations, psychotic episodes, confusion, and paranoia. Because of the uncontrolled nature of many of the studies, it is impossible to provide a precise estimate of the extent of risk imposed by treatment with clomipramine hydrochloride capsules. As with tricyclic antidepressants to which they are closely related, clomipramine hydrochloride capsules may precipitate an acute psychotic episode in patients with unrecognized schizophrenia.

Mania/Hypomania – During premarketing testing of clomipramine hydrochloride capsules in patients with affective disorder, hypomania or mania was precipitated in several patients. Activation of mania or hypomania has also been reported in a small proportion of patients with affective disorder treated with marketed tricyclic antidepressants, which are closely related to clomipramine hydrochloride capsules.

Hepatic Changes – During premarketing testing, clomipramine hydrochloride capsules were occasionally associated with elevations in SGOT and SGPT (pooled incidence of approximately 1% and 3%, respectively) of potential clinical importance (i.e., values greater than 3 times the upper limit of normal). In the vast majority of instances, these enzyme increases were not associated with other clinical findings suggestive of hepatic injury; moreover, none were jaundiced. Rare reports of more severe liver injury, some fatal, have been recorded in foreign postmarketing experience. Caution is indicated in treating patients with known liver disease, and periodic monitoring of hepatic enzyme levels is recommended in such patients.

Hematologic Changes – Although no instances of severe hematologic toxicity were seen in the premarketing experience with clomipramine hydrochloride capsules, there have been postmarketing reports of leukopenia, agranulocytosis, thrombocytopenia, anemia, and pancytopenia in association with clomipramine hydrochloride capsules use. As is the case with tricyclic antidepressants to which clomipramine hydrochloride capsules are closely related, leukocyte and differential blood counts should be obtained in patients who develop fever and sore throat during treatment with clomipramine hydrochloride capsules.

Central Nervous System – More than 30 cases of hyperthermia have been recorded by nondomestic postmarketing surveillance systems. Most cases occurred when clomipramine hydrochloride capsules were used in combination with other drugs. When clomipramine hydrochloride capsules and a neuroleptic were used concomitantly, the cases were sometimes considered to be examples of a neuroleptic malignant syndrome.

Sexual Dysfunction – The rate of sexual dysfunction in male patients with OCD who were treated with clomipramine hydrochloride capsules in the premarketing experience was markedly increased compared with placebo controls (i.e., 42% experienced ejaculatory failure and 20% experienced impotence, compared with 2.0% and 2.6%, respectively, in the placebo group). Approximately 85% of males with sexual dysfunction chose to continue treatment.

Hyponatremia – Hyponatremia has occurred as a result of treatment with clomipramine. In many cases, hyponatremia appears to be the result of the syndrome of inappropriate antidiuretic hormone secretion (SIADH). Elderly patients may be at greater risk of developing hyponatremia with a serotonergic antidepressant. Also, patients taking diuretics or who are otherwise volume-depleted can be at greater risk. Discontinuation of clomipramine hydrochloride capsules in patients with symptomatic hyponatremia and appropriate medical intervention should be instituted. Signs and symptoms of hyponatremia include headache, difficulty concentrating, memory impairment, confusion, weakness, and unsteadiness, which can lead to falls. More severe and/or acute cases have included hallucination, syncope, seizure, coma, respiratory arrest, and death.

Weight Changes – In controlled studies of OCD, weight gain was reported in 18% of patients receiving clomipramine hydrochloride capsules, compared with 1% of patients receiving placebo. In these studies, 28% of patients receiving clomipramine hydrochloride capsules had a weight gain of at least 7% of their initial body weight, compared with 4% of patients receiving placebo. Several patients had weight gains in excess of 25% of their initial body weight. Conversely, 5% of patients receiving clomipramine hydrochloride capsules and 1% receiving placebo had weight losses of at least 7% of their initial body weight.

Electroconvulsive Therapy – As with closely related tricyclic antidepressants, concurrent administration of clomipramine hydrochloride capsules with electroconvulsive therapy may increase the risks; such treatment should be limited to those patients for whom it is essential, since there is limited clinical experience.

Surgery – Prior to elective surgery with general anesthetics, therapy with clomipramine hydrochloride capsules should be discontinued for as long as is clinically feasible, and the anesthetist should be advised.

Use in Concomitant Illness – As with closely related tricyclic antidepressants, clomipramine hydrochloride capsules should be used with caution in the following:

(1) Hyperthyroid patients or patients receiving thyroid medication, because of the possibility of cardiac toxicity;

(2) Patients with increased intraocular pressure, a history of narrow-angle glaucoma, or urinary retention, because of the anticholinergic properties of the drug;

(3) Patients with tumors of the adrenal medulla (e.g., pheochromocytoma, neuroblastoma) in whom the drug may provoke hypertensive crises;

(4) Patients with significantly impaired renal function.

Withdrawal Symptoms – A variety of withdrawal symptoms have been reported in association with abrupt discontinuation of clomipramine hydrochloride capsules, including dizziness, nausea, vomiting, headache, malaise, sleep disturbance, hyperthermia, and irritability. In addition, such patients may experience a worsening of psychiatric status. While the withdrawal effects of clomipramine hydrochloride capsules have not been systematically evaluated in controlled trials, they are well known with closely related tricyclic antidepressants, and it is recommended that the dosage be tapered gradually and the patient monitored carefully during discontinuation (see DRUG ABUSE AND DEPENDENCE).

Information for Patients

Prescribers or other health professionals should inform patients, their families, and their caregivers about the benefits and risks associated with treatment with clomipramine hydrochloride and should counsel them in its appropriate use. A patient Medication Guide about “Antidepressant Medicines, Depression and other Serious Mental Illness, and Suicidal Thoughts or Actions” is available for clomipramine hydrochloride. The prescriber or health professional should instruct patients, their families, and their caregivers to read the Medication Guide and should assist them in understanding its contents. Patients should be given the opportunity to discuss the contents of the Medication Guide and to obtain answers to any questions they may have. The complete text of the Medication Guide is reprinted at the end of this document.

Patients should be advised of the following issues and asked to alert their prescriber if these occur while taking clomipramine hydrochloride.

Clinical Worsening and Suicide Risk – Patients, their families, and their caregivers should be encouraged to be alert to the emergence of anxiety, agitation, panic attacks, insomnia, irritability, hostility, aggressiveness, impulsivity, akathisia (psychomotor restlessness), hypomania, mania, other unusual changes in behavior, worsening of depression, and suicidal ideation, especially early during antidepressant treatment and when the dose is adjusted up or down. Families and caregivers of patients should be advised to look for the emergence of such symptoms on a day-to-day basis, since changes may be abrupt. Such symptoms should be reported to the patient’s prescriber or health professional, especially if they are severe, abrupt in onset, or were not part of the patient’s presenting symptoms. Symptoms such as these may be associated with an increased risk for suicidal thinking and behavior and indicate a need for very close monitoring and possibly changes in the medication.

Physicians are advised to discuss the following issues with patients for whom they prescribe clomipramine hydrochloride capsules:

(1) The risk of seizure (see WARNINGS);

(2) The relatively high incidence of sexual dysfunction among males (see Sexual Dysfunction);

(3) Since clomipramine hydrochloride capsules may impair the mental and/or physical abilities required for the performance of complex tasks, and since clomipramine hydrochloride capsules are associated with a risk of seizures, patients should be cautioned about the performance of complex and hazardous tasks (see WARNINGS);

(4) Patients should be cautioned about using alcohol, barbiturates, or other CNS depressants concurrently, since clomipramine hydrochloride capsules may exaggerate their response to these drugs;

(5) Patients should notify their physician if they become pregnant or intend to become pregnant during therapy;

(6) Patients should notify their physician if they are breast-feeding.

Patients should be advised that taking clomipramine hydrochloride capsules can cause mild pupillary dilation, which in susceptible individuals, can lead to an episode of angle-closure glaucoma. Pre-existing glaucoma is almost always open-angle glaucoma because angle-closure glaucoma, when diagnosed, can be treated definitively with iridectomy. Open-angle glaucoma is not a risk factor for angle-closure glaucoma. Patients may wish to be examined to determine whether they are susceptible to angle closure, and have a prophylactic procedure (e.g., iridectomy), if they are susceptible.

Drug Interactions

The risks of using clomipramine hydrochloride capsules in combination with other drugs have not been systematically evaluated. Given the primary CNS effects of clomipramine hydrochloride capsules, caution is advised in using them concomitantly with other CNS-active drugs (see Information for Patients). Clomipramine hydrochloride capsules should not be used with MAO inhibitors (see CONTRAINDICATIONS).

Close supervision and careful adjustment of dosage are required when clomipramine hydrochloride capsules are administered with anticholinergic or sympathomimetic drugs.

Several tricyclic antidepressants have been reported to block the pharmacologic effects of guanethidine, clonidine, or similar agents, and such an effect may be anticipated with CMI because of its structural similarity to other tricyclic antidepressants.

The plasma concentration of CMI has been reported to be increased by the concomitant administration of haloperidol; plasma levels of several closely related tricyclic antidepressants have been reported to be increased by the concomitant administration of methylphenidate or hepatic enzyme inhibitors (e.g., cimetidine, fluoxetine) and decreased by the concomitant administration of hepatic enzyme inducers (e.g., barbiturates, phenytoin), and such an effect may be anticipated with CMI as well. Administration of CMI has been reported to increase the plasma levels of phenobarbital, if given concomitantly (see CLINICAL PHARMACOLOGY, Interactions).

Drugs Metabolized by P450 2D6 – The biochemical activity of the drug metabolizing isozyme cytochrome P450 2D6 (debrisoquin hydroxylase) is reduced in a subset of the Caucasian population (about 7% to 10% of Caucasians are so-called “poor metabolizers”); reliable estimates of the prevalence of reduced P450 2D6 isozyme activity among Asian, African and other populations are not yet available. Poor metabolizers have higher than expected plasma concentrations of tricyclic antidepressants (TCAs) when given usual doses. Depending on the fraction of drug metabolized by P450 2D6, the increase in plasma concentration may be small, or quite large (8 fold increase in plasma AUC of the TCA). In addition, certain drugs inhibit the activity of this isozyme and make normal metabolizers resemble poor metabolizers. An individual who is stable on a given dose of TCA may become abruptly toxic when given one of these inhibiting drugs as concomitant therapy. The drugs that inhibit cytochrome P450 2D6 include some that are not metabolized by the enzyme (quinidine; cimetidine) and many that are substrates for P450 2D6 (many other antidepressants, phenothiazines, and the Type 1C antiarrhythmics propafenone and flecainide). While all the selective serotonin reuptake inhibitors (SSRIs), e.g., fluoxetine, sertraline, paroxetine, and fluvoxamine, inhibit P450 2D6, they may vary in the extent of inhibition. Fluvoxamine has also been shown to inhibit P450 1A2, an isoform also involved in TCA metabolism. The extent to which SSRI-TCA interactions may pose clinical problems will depend on the degree of inhibition and the pharmacokinetics of the SSRI involved. Nevertheless, caution is indicated in the co-administration of TCAs with any of the SSRIs and also in switching from one class to the other. Of particular importance, sufficient time must elapse before initiating TCA treatment in a patient being withdrawn from fluoxetine, given the long half-life of the parent and active metabolite (at least
5 weeks may be necessary). Concomitant use of agents in the tricyclic antidepressant class (which includes clomipramine hydrochloride capsules) with drugs that can inhibit cytochrome P450 2D6 may require lower doses than usually prescribed for either the tricyclic antidepressant agent or the other drug. Furthermore, whenever one of these drugs is withdrawn from co-therapy, an increased dose of tricyclic antidepressant agent may be required. It is desirable to monitor TCA plasma levels whenever an agent of the tricyclic antidepressant class including clomipramine hydrochloride capsules is going to be co-administered with another drug known to be an inhibitor of P450 2D6 (and/or P450 1A2).

Because clomipramine hydrochloride capsules are highly bound to serum protein, the administration of clomipramine hydrochloride capsules to patients taking other drugs that are highly bound to protein (e.g., warfarin, digoxin) may cause an increase in plasma concentrations of these drugs, potentially resulting in adverse effects. Conversely, adverse effects may result from displacement of protein-bound clomipramine hydrochloride capsules by other highly bound drugs (see CLINICAL PHARMACOLOGY, Distribution).

Monoamine Oxidase Inhibitors (MAOIs)

(See CONTRAINDICATIONS, WARNINGS, and DOSAGE AND ADMINISTRATION.)

Serotonergic Drugs

(See CONTRAINDICATIONS, WARNINGS, and DOSAGE AND ADMINISTRATION.)

Carcinogenesis, Mutagenesis, Impairment of Fertility

No evidence of carcinogenicity was found in two 2-year bioassays in rats at doses up to 100 mg/kg, which is 24 and 4 times the maximum recommended human daily dose (MRHD) on a mg/kg and mg/m^2 basis, respectively, or in a 2-year bioassay in mice at doses up to 80 mg/kg, which is 20 and 1.5 times the MRHD on a mg/kg and mg/m^2 basis, respectively.

In reproduction studies, no effects on fertility were found in rats given up to 24 mg/kg, which is 6 times, and approximately equal to, the MRHD on a mg/kg and mg/m^2 basis, respectively.

Pregnancy Category C

No teratogenic effects were observed in studies performed in rats and mice at doses up to 100 mg/kg, which is 24 times the maximum recommended human daily dose (MRHD) on a mg/kg basis and 4 times (rats) and 2 times (mice) the MRHD on a mg/m^2 basis. Slight nonspecific embryo/fetotoxic effects were seen in the offspring of treated rats given 50 and 100 mg/kg and of treated mice given 100 mg/kg.

There are no adequate or well-controlled studies in pregnant women. Withdrawal symptoms, including jitteriness, tremor, and seizures, have been reported in neonates whose mothers had taken clomipramine hydrochloride capsules until delivery. Clomipramine hydrochloride capsules should be used during pregnancy only if the potential benefit justifies the potential risk to the fetus.

Nursing Mothers

Clomipramine hydrochloride has been found in human milk. Because of the potential for adverse reactions, a decision should be made whether to discontinue nursing or to discontinue the drug, taking into account the importance of the drug to the mother.

Pediatric Use

Safety and effectiveness in the pediatric population other than pediatric patients with OCD have not been established (see BOX WARNING and WARNINGS, Clinical Worsening and Suicide Risk). Anyone considering the use of clomipramine hydrochloride capsules in a child or adolescent must balance the potential risks with the clinical need.

In a controlled clinical trial in children and adolescents (10 to 17 years of age), 46 outpatients received clomipramine hydrochloride capsules for up to 8 weeks. In addition, 150 adolescent patients have received clomipramine hydrochloride capsules in open-label protocols for periods of several months to several years. Of the 196 adolescents studied, 50 were 13 years of age or less and 146 were 14 to 17 years of age. The adverse reaction profile in this age group (see ADVERSE REACTIONS) is similar to that observed in adults.

The risks, if any, that may be associated with clomipramine hydrochloride capsules’ extended use in children and adolescents with OCD have not been systematically assessed. The evidence supporting the conclusion that clomipramine hydrochloride capsules are safe for use in children and adolescents is derived from relatively short term clinical studies and from extrapolation of experience gained with adult patients. In particular, there are no studies that directly evaluate the effects of long term clomipramine hydrochloride capsules use on the growth, development, and maturation of children and adolescents. Although there is no evidence to suggest that clomipramine hydrochloride capsules adversely affect growth, development or maturation, the absence of such findings is not adequate to rule out a potential for such effects in chronic use.

The safety and effectiveness in pediatric patients below the age of 10 have not been established. Therefore, specific recommendations cannot be made for the use of clomipramine hydrochloride capsules in pediatric patients under the age of 10.

Geriatric Use

Clinical studies of clomipramine hydrochloride capsules did not include sufficient numbers of subjects age 65 and over to determine whether they respond differently from younger subjects; 152 patients at least 60 years of age participating in various U.S. clinical trials received clomipramine hydrochloride capsules for periods of several months to several years. No unusual age-related adverse events were identified in this population. Other reported clinical experience has not identified differences in responses between the elderly and younger patients. In general, dose selection for an elderly patient should be cautious, usually starting at the low end of the dosing range, reflecting the greater frequency of decreased hepatic, renal, or cardiac function and of concomitant disease or other drug therapy.

Clomipramine hydrochloride capsules have been associated with cases of clinically significant hyponatremia. Elderly patients may be at greater risk for this adverse reaction (see PRECAUTIONS, Hyponatremia).

ADVERSE REACTIONS

Commonly Observed

The most commonly observed adverse events associated with the use of clomipramine hydrochloride capsules and not seen at an equivalent incidence among placebo-treated patients were gastrointestinal complaints, including dry mouth, constipation, nausea, dyspepsia, and anorexia; nervous system complaints, including somnolence, tremor, dizziness, nervousness, and myoclonus; genitourinary complaints, including changed libido, ejaculatory failure, impotence, and micturition disorder; and other miscellaneous complaints, including fatigue, sweating, increased appetite, weight gain, and visual changes.

Leading to Discontinuation of Treatment

Approximately 20% of 3616 patients who received clomipramine hydrochloride capsules in U.S. premarketing clinical trials discontinued treatment because of an adverse event. Approximately one-half of the patients who discontinued (9% of the total) had multiple complaints, none of which could be classified as primary. Where a primary reason for discontinuation could be identified, most patients discontinued because of nervous system complaints (5.4%), primarily somnolence. The second-most-frequent reason for discontinuation was digestive system complaints (1.3%), primarily vomiting and nausea.

There was no apparent relationship between the adverse events and elevated plasma drug concentrations.

Incidence in Controlled Clinical Trials

The following table enumerates adverse events that occurred at an incidence of 1% or greater among patients with OCD who received clomipramine hydrochloride capsules in adult or pediatric placebo-controlled clinical trials. The frequencies were obtained from pooled data of clinical trials involving either adults receiving clomipramine hydrochloride capsules (N=322) or placebo (N=319) or children treated with clomipramine hydrochloride capsules (N=46) or placebo (N=44). The prescriber should be aware that these figures cannot be used to predict the incidence of side effects in the course of usual medical practice, in which patient characteristics and other factors differ from those that prevailed in the clinical trials. Similarly, the cited frequencies cannot be compared with figures obtained from other clinical investigations involving different treatments, uses, and investigators. The cited figures, however, provide the physician with a basis for estimating the relative contribution of drug and nondrug factors to the incidence of side effects in the populations studied.

Incidence of Treatment-Emergent Adverse Experience
in Placebo-Controlled Clinical Trials
(Percentage of Patients Reporting Event)

 | Adults |  |  | Children and Adolescents
Body System/ Adverse Event* | Clomipramine Hydrochloride Capsules (N=322) | Placebo (N=319) |  | Clomipramine Hydrochloride Capsules (N=46) | Placebo (N=44)
Nervous System
Somnolence | 54 | 16 |  | 46 | 11
Tremor | 54 | 2 |  | 33 | 2
Dizziness | 54 | 14 |  | 41 | 14
Headache | 52 | 41 |  | 28 | 34
Insomnia | 25 | 15 |  | 11 | 7
Libido change | 21 | 3 |  | - | -
Nervousness | 18 | 2 |  | 4 | 2
Myoclonus | 13 | - |  | 2 | -
Increased appetite | 11 | 2 |  | - | 2
Paresthesia | 9 | 3 |  | 2 | 2
Memory impairment | 9 | 1 |  | 7 | 2
Anxiety | 9 | 4 |  | 2 | -
Twitching | 7 | 1 |  | 4 | 5
Impaired concentration | 5 | 2 |  | - | -
Depression | 5 | 1 |  | - | -
Hypertonia | 4 | 1 |  | 2 | -
Sleep disorder | 4 | - |  | 9 | 5
Psychosomatic disorder | 3 | - |  | - | -
Yawning | 3 | - |  | - | -
Confusion | 3 | - |  | 2 | -
Speech disorder | 3 | - |  | - | -
Abnormal dreaming | 3 | - |  | - | 2
Agitation | 3 | - |  | - | -
Migraine | 3 | - |  | - | -
Depersonalization | 2 | - |  | 2 | -
Irritability | 2 | 2 |  | 2 | -
Emotional lability | 2 | - |  | - | 2
Panic reaction | 1 | - |  | 2 | -
Aggressive reaction | - | - |  | 2 | -
Paresis | - | - |  | 2 | -
Skin and Appendages
Increased sweating | 29 | 3 |  | 9 | -
Rash | 8 | 1 |  | 4 | 2
Pruritus | 6 | - |  | 2 | 2
Dermatitis | 2 | - |  | - | 2
Acne | 2 | 2 |  | - | 5
Dry skin | 2 | - |  | - | 5
Urticaria | 1 | - |  | - | -
Abnormal skin odor | - | - |  | 2 | -
Digestive System
Dry mouth | 84 | 17 |  | 63 | 16
Constipation | 47 | 11 |  | 22 | 9
Nausea | 33 | 14 |  | 9 | 11
Dyspepsia | 22 | 10 |  | 13 | 2
Diarrhea | 13 | 9 |  | 7 | 5
Anorexia | 12 | - |  | 22 | 2
Abdominal pain | 11 | 9 |  | 13 | 16
Vomiting | 7 | 2 |  | 7 | -
Flatulence | 6 | 3 |  | - | 2
Tooth disorder | 5 | - |  | - | -
Gastrointestinal disorder | 2 | - |  | - | 2
Dysphagia | 2 | - |  | - | -
Esophagitis | 1 | - |  | - | -
Eructation | - | - |  | 2 | 2
Ulcerative stomatitis | - | - |  | 2 | -
Body as a Whole
Fatigue | 39 | 18 |  | 35 | 9
Weight increase | 18 | 1 |  | 2 | -
Flushing | 8 | - |  | 7 | -
Hot flushes | 5 | - |  | 2 | -
Chest pain | 4 | 4 |  | 7 | -
Fever | 4 | - |  | 2 | 7
Allergy | 3 | 3 |  | 7 | 5
Pain | 3 | 2 |  | 4 | 2
Local edema | 2 | 4 |  | - | -
Chills | 2 | 1 |  | - | -
Weight decrease | - | - |  | 7 | -
Otitis media | - | - |  | 4 | 5
Asthenia | - | - |  | 2 | -
Halitosis | - | - |  | 2 | -
Cardiovascular System
Postural hypotension | 6 | - |  | 4 | -
Palpitation | 4 | 2 |  | 4 | -
Tachycardia | 4 | - |  | 2 | -
Syncope | - | - |  | 2 | -
Respiratory System
Pharyngitis | 14 | 9 |  | - | 5
Rhinitis | 12 | 10 |  | 7 | 9
Sinusitis | 6 | 4 |  | 2 | 5
Coughing | 6 | 6 |  | 4 | 5
Bronchospasm | 2 | - |  | 7 | 2
Epistaxis | 2 | - |  | - | 2
Dyspnea | - | - |  | 2 | -
Laryngitis | - | 1 |  | 2 | -
Urogenital System
Male and Female Patients Combined
Micturition disorder | 14 | 2 |  | 4 | 2
Urinary tract infection | 6 | 1 |  | - | -
Micturition frequency | 5 | 3 |  | - | -
Urinary retention | 2 | - |  | 7 | -
Dysuria | 2 | 2 |  | - | -
Cystitis | 2 | - |  | - | -
Female Patients Only | (N=182) | (N=167) |  | (N=10) | (N=21)
Dysmenorrhea | 12 | 14 |  | 10 | 10
Lactation (nonpuerperal) | 4 | - |  | - | -
Menstrual disorder | 4 | 2 |  | - | -
Vaginitis | 2 | - |  | - | -
Leukorrhea | 2 | - |  | - | -
Breast enlargement | 2 | - |  | - | -
Breast pain | 1 | - |  | - | -
Amenorrhea | 1 | - |  | - | -
Male Patients Only | (N=140) | (N=152) |  | (N=36) | (N=23)
Ejaculation failure | 42 | 2 |  | 6 | -
Impotence | 20 | 3 |  | - | -
Special Senses
Abnormal vision | 18 | 4 |  | 7 | 2
Taste perversion | 8 | - |  | 4 | -
Tinnitus | 6 | - |  | 4 | -
Abnormal lacrimation | 3 | 2 |  | - | -
Mydriasis | 2 | - |  | - | -
Conjunctivitis | 1 | - |  | - | -
Anisocoria | - | - |  | 2 | -
Blepharospasm | - | - |  | 2 | -
Ocular allergy | - | - |  | 2 | -
Vestibular disorder | - | - |  | 2 | 2
Musculoskeletal
Myalgia | 13 | 9 |  | - | -
Back pain | 6 | 6 |  | - | -
Arthralgia | 3 | 5 |  | - | -
Muscle weakness | 1 | - |  | 2 | -
Hemic and Lymphatic
Purpura | 3 | - |  | - | -
Anemia | - | - |  | 2 | 2
Metabolic and Nutritional
Thirst | 2 | 2 |  | - | 2

*Events reported by at least 1% of clomipramine hydrochloride capsules patients are included.

Other Events Observed During the Premarketing Evaluation of Clomipramine Hydrochloride Capsules

During clinical testing in the U.S., multiple doses of clomipramine hydrochloride capsules were administered to approximately 3600 subjects. Untoward events associated with this exposure were recorded by clinical investigators using terminology of their own choosing. Consequently, it is not possible to provide a meaningful estimate of the proportion of individuals experiencing adverse events without first grouping similar types of untoward events into a smaller number of standardized event categories.

In the tabulations that follow, a modified World Health Organization dictionary of terminology has been used to classify reported adverse events. The frequencies presented, therefore, represent the proportion of the 3525 individuals exposed to clomipramine hydrochloride capsules who experienced an event of the type cited on at least one occasion while receiving clomipramine hydrochloride capsules. All events are included except those already listed in the previous table, those reported in terms so general as to be uninformative, and those in which an association with the drug was remote. It is important to emphasize that although the events reported occurred during treatment with clomipramine hydrochloride capsules, they were not necessarily caused by it.

Events are further categorized by body system and listed in order of decreasing frequency according to the following definitions: frequent adverse events are those occurring on one or more occasions in at least 1/100 patients; infrequent adverse events are those occurring in 1/100 to 1/1000 patients; rare events are those occurring in less than 1/1000 patients.

Body as a Whole – Infrequent - general edema, increased susceptibility to infection, malaise. Rare - dependent edema, withdrawal syndrome.

Cardiovascular System – Infrequent - abnormal ECG, arrhythmia, bradycardia, cardiac arrest, extrasystoles, pallor. Rare - aneurysm, atrial flutter, bundle branch block, cardiac failure, cerebral hemorrhage, heart block, myocardial infarction, myocardial ischemia, peripheral ischemia, thrombophlebitis, vasospasm, ventricular tachycardia.

Digestive System – Infrequent - abnormal hepatic function, blood in stool, colitis, duodenitis, gastric ulcer, gastritis, gastroesophageal reflux, gingivitis, glossitis, hemorrhoids, hepatitis, increased saliva, irritable bowel syndrome, peptic ulcer, rectal hemorrhage, tongue ulceration, tooth caries. Rare - cheilitis, chronic enteritis, discolored feces, gastric dilatation, gingival bleeding, hiccup, intestinal obstruction, oral/pharyngeal edema, paralytic ileus, salivary gland enlargement.

Endocrine System – Infrequent - hypothyroidism. Rare - goiter, gynecomastia, hyperthyroidism.

Hemic and Lymphatic System – Infrequent - lymphadenopathy. Rare - leukemoid reaction, lymphoma-like disorder, marrow depression.

Metabolic and Nutritional Disorder – Infrequent - dehydration, diabetes mellitus, gout, hypercholesterolemia, hyperglycemia, hyperuricemia, hypokalemia. Rare - fat intolerance, glycosuria.

Musculoskeletal System – Infrequent - arthrosis. Rare - dystonia, exostosis, lupus erythematosus rash, bruising, myopathy, myositis, polyarteritis nodosa, torticollis.

Nervous System – Frequent - abnormal thinking, vertigo. Infrequent - abnormal coordination, abnormal EEG, abnormal gait, apathy, ataxia, coma, convulsions, delirium, delusion, dyskinesia, dysphonia, encephalopathy, euphoria, extrapyramidal disorder, hallucinations, hostility, hyperkinesia, hypnagogic hallucinations, hypokinesia, leg cramps, manic reaction, neuralgia, paranoia, phobic disorder, psychosis, sensory disturbance, somnambulism, stimulation, suicidal ideation, suicide attempt, teeth-grinding. Rare - anticholinergic syndrome, aphasia, apraxia, catalepsy, cholinergic syndrome, choreoathetosis, generalized spasm, hemiparesis, hyperesthesia, hyperreflexia, hypoesthesia, illusion, impaired impulse control, indecisiveness, mutism, neuropathy, nystagmus, oculogyric crisis, oculomotor nerve paralysis, schizophrenic reaction, stupor, suicide.

Respiratory System – Infrequent - bronchitis, hyperventilation, increased sputum, pneumonia. Rare - cyanosis, hemoptysis, hypoventilation, laryngismus.

Skin and Appendages – Infrequent - alopecia, cellulitis, cyst, eczema, erythematous rash, genital pruritus, maculopapular rash, photosensitivity reaction, psoriasis, pustular rash, skin discoloration. Rare - chloasma, folliculitis, hypertrichosis, piloerection, seborrhea, skin hypertrophy, skin ulceration.

Special Senses – Infrequent - abnormal accommodation, deafness, diplopia, earache, eye pain, foreign body sensation, hyperacusis, parosmia, photophobia, scleritis, taste loss. Rare - blepharitis, chromatopsia, conjunctival hemorrhage, exophthalmos, glaucoma, keratitis, labyrinth disorder, night blindness, retinal disorder, strabismus, visual field defect.

Urogenital System – Infrequent - endometriosis, epididymitis, hematuria, nocturia, oliguria, ovarian cyst, perineal pain, polyuria, prostatic disorder, renal calculus, renal pain, urethral disorder, urinary incontinence, uterine hemorrhage, vaginal hemorrhage. Rare - albuminuria, anorgasmy, breast engorgement, breast fibroadenosis, cervical dysplasia, endometrial hyperplasia, premature ejaculation, pyelonephritis, pyuria, renal cyst, uterine inflammation, vulvar disorder.

Postmarketing Experience

The following adverse drug reaction has been reported during post-approval use of clomipramine hydrochloride capsules. Because this reaction is reported voluntarily from a population of uncertain size, it is not always possible to reliably estimate frequency.

Eye Disorders – Angle-closure glaucoma.

Immune System Disorders – Drug Rash with Eosinophilia and Systemic Symptoms (DRESS).

Metabolism and Nutrition Disorders – Hyponatremia.

Endocrine Disorders – Syndrome of inappropriate antidiuretic hormone secretion (SIADH).

DRUG ABUSE AND DEPENDENCE

Clomipramine hydrochloride capsules have not been systematically studied in animals or humans for its potential for abuse, tolerance, or physical dependence. While a variety of withdrawal symptoms have been described in association with clomipramine hydrochloride capsules discontinuation (see PRECAUTIONS, Withdrawal Symptoms), there is no evidence for drug-seeking behavior, except for a single report of potential clomipramine hydrochloride capsules abuse by a patient with a history of dependence on codeine, benzodiazepines, and multiple psychoactive drugs. The patient received clomipramine hydrochloride capsules for depression and panic attacks and appeared to become dependent after hospital discharge.

Despite the lack of evidence suggesting an abuse liability for clomipramine hydrochloride capsules in foreign marketing, it is not possible to predict the extent to which clomipramine hydrochloride capsules might be misused or abused once marketed in the U.S. Consequently, physicians should carefully evaluate patients for a history of drug abuse and follow such patients closely.

OVERDOSAGE

Deaths may occur from overdosage with this class of drugs. Multiple drug ingestion (including alcohol) is common in deliberate tricyclic overdose. As the management is complex and changing, it is recommended that the physician contact a poison control center for current information on treatment. Signs and symptoms of toxicity develop rapidly after tricyclic overdose. Therefore, hospital monitoring is required as soon as possible.

Human Experience

In U.S. clinical trials, 2 deaths occurred in 12 reported cases of acute overdosage with clomipramine hydrochloride capsules either alone or in combination with other drugs. One death involved a patient suspected of ingesting a dose of 7000 mg. The second death involved a patient suspected of ingesting a dose of 5750 mg. The 10 nonfatal cases involved doses of up to 5000 mg, accompanied by plasma levels of up to 1010 ng/mL. All 10 patients completely recovered. Among reports from other countries of clomipramine hydrochloride capsules overdose, the lowest dose associated with a fatality was 750 mg. Based upon postmarketing reports in the United Kingdom, CMI’s lethality in overdose is considered to be similar to that reported for closely related tricyclic compounds marketed as antidepressants.

Manifestations

Signs and symptoms vary in severity depending upon factors such as the amount of drug absorbed, the age of the patient, and the time elapsed since drug ingestion. Critical manifestations of overdose include cardiac dysrhythmias, severe hypotension, convulsions, and CNS depression including coma. Changes in the electrocardiogram, particularly in QRS axis or width, are clinically significant indicators of tricyclic toxicity. Other CNS manifestations may include drowsiness, stupor, ataxia, restlessness, agitation, delirium, severe perspiration, hyperactive reflexes, muscle rigidity, and athetoid and choreiform movements. Cardiac abnormalities may include tachycardia, signs of congestive heart failure, and in very rare cases, cardiac arrest. Respiratory depression, cyanosis, shock, vomiting, hyperpyrexia, mydriasis, and oliguria or anuria may also be present.

Management

Obtain an ECG and immediately initiate cardiac monitoring. Protect the patient’s airway, establish an intravenous line, and initiate gastric decontamination. A minimum of 6 hours of observation with cardiac monitoring and observation for signs of CNS or respiratory depression, hypotension, cardiac dysrhythmias and/or conduction blocks, and seizures is necessary.

If signs of toxicity occur at any time during this period, extended monitoring is required. There are case reports of patients succumbing to fatal dysrhythmias late after overdose; these patients had clinical evidence of significant poisoning prior to death and most received inadequate gastrointestinal decontamination. Monitoring of plasma drug levels should not guide management of the patient.

Gastrointestinal Decontamination – All patients suspected of tricyclic overdose should receive gastrointestinal decontamination. This should include large volume gastric lavage followed by activated charcoal. If consciousness is impaired, the airway should be secured prior to lavage. Emesis is contraindicated.

Cardiovascular – A maximal limb-lead QRS duration of ≥ 0.10 seconds may be the best indication of the severity of the overdose. Intravenous sodium bicarbonate should be used to maintain the serum pH in the range of 7.45 to 7.55. If the pH response is inadequate, hyperventilation may also be used. Concomitant use of hyperventilation and sodium bicarbonate should be done with extreme caution, with frequent pH monitoring. A pH >7.60 or a pCO2 <20 mmHg is undesirable. Dysrhythmias unresponsive to sodium bicarbonate therapy/hyperventilation may respond to lidocaine, bretylium, or phenytoin. Type 1A and 1C antiarrhythmics are generally contraindicated (e.g., quinidine, disopyramide, and procainamide).

In rare instances, hemoperfusion may be beneficial in acute refractory cardiovascular instability in patients with acute toxicity. However, hemodialysis, peritoneal dialysis, exchange transfusions, and forced diuresis generally have been reported as ineffective in tricyclic poisoning.

CNS – In patients with CNS depression, early intubation is advised because of the potential for abrupt deterioration. Seizures should be controlled with benzodiazepines, or if these are ineffective, other anticonvulsants (e.g., phenobarbital, phenytoin). Physostigmine is not recommended except to treat life-threatening symptoms that have been unresponsive to other therapies, and then only in consultation with a poison control center.

Psychiatric Follow-up – Since overdosage is often deliberate, patients may attempt suicide by other means during the recovery phase. Psychiatric referral may be appropriate.

Pediatric Management – The principles of management of child and adult overdosages are similar. It is strongly recommended that the physician contact the local poison control center for specific pediatric treatment.

DOSAGE AND ADMINISTRATION

The treatment regimens described below are based on those used in controlled clinical trials of clomipramine hydrochloride capsules in 520 adults, and 91 children and adolescents with OCD. During initial titration, clomipramine hydrochloride capsules should be given in divided doses with meals to reduce gastrointestinal side effects. The goal of this initial titration phase is to minimize side effects by permitting tolerance to side effects to develop or allowing the patient time to adapt if tolerance does not develop.

Because both CMI and its active metabolite, DMI, have long elimination half-lives, the prescriber should take into consideration the fact that steady-state plasma levels may not be achieved until 2 to 3 weeks after dosage change (see CLINICAL PHARMACOLOGY). Therefore, after initial titration, it may be appropriate to wait 2 to 3 weeks between further dosage adjustments.

Initial Treatment/Dose Adjustment (Adults)

Treatment with clomipramine hydrochloride capsules should be initiated at a dosage of 25 mg daily and gradually increased, as tolerated, to approximately 100 mg during the first 2 weeks. During initial titration, clomipramine hydrochloride capsules should be given in divided doses with meals to reduce gastrointestinal side effects. Thereafter, the dosage may be increased gradually over the next several weeks, up to a maximum of 250 mg daily. After titration, the total daily dose may be given once daily at bedtime to minimize daytime sedation.

Initial Treatment/Dose Adjustment (Children and Adolescents)

As with adults, the starting dose is 25 mg daily and should be gradually increased (also given in divided doses with meals to reduce gastrointestinal side effects) during the first 2 weeks, as tolerated, up to a daily maximum of 3 mg/kg or 100 mg, whichever is smaller. Thereafter, the dosage may be increased gradually over the next several weeks up to a daily maximum of 3 mg/kg or 200 mg, whichever is smaller (see PRECAUTIONS, Pediatric Use). As with adults, after titration, the total daily dose may be given once daily at bedtime to minimize daytime sedation.

Maintenance/Continuation Treatment (Adults, Children, and Adolescents)

While there are no systematic studies that answer the question of how long to continue clomipramine hydrochloride capsules, OCD is a chronic condition and it is reasonable to consider continuation for a responding patient. Although the efficacy of clomipramine hydrochloride capsules after 10 weeks has not been documented in controlled trials, patients have been continued in therapy under double-blind conditions for up to 1 year without loss of benefit. However, dosage adjustments should be made to maintain the patient on the lowest effective dosage, and patients should be periodically reassessed to determine the need for treatment. During maintenance, the total daily dose may be given once daily at bedtime.

Switching a Patient To or From a Monoamine Oxidase Inhibitor (MAOI) Intended to Treat Psychiatric Disorders

At least 14 days should elapse between discontinuation of an MAOI intended to treat psychiatric disorders and initiation of therapy with clomipramine hydrochloride capsules. Conversely, at least 14 days should be allowed after stopping clomipramine hydrochloride capsules before starting an MAOI intended to treat psychiatric disorders (see CONTRAINDICATIONS).

Use of Clomipramine Hydrochloride Capsules With Other MAOIs, Such as Linezolid or Methylene Blue

Do not start clomipramine hydrochloride capsules in a patient who is being treated with linezolid or intravenous methylene blue because there is increased risk of serotonin syndrome. In a patient who requires more urgent treatment of a psychiatric condition, other interventions, including hospitalization, should be considered (see CONTRAINDICATIONS).

In some cases, a patient already receiving clomipramine hydrochloride capsules therapy may require urgent treatment with linezolid or intravenous methylene blue. If acceptable alternatives to linezolid or intravenous methylene blue treatment are not available and the potential benefits of linezolid or intravenous methylene blue treatment are judged to outweigh the risks of serotonin syndrome in a particular patient, clomipramine hydrochloride capsules should be stopped promptly, and linezolid or intravenous methylene blue can be administered. The patient should be monitored for symptoms of serotonin syndrome for two weeks or until 24 hours after the last dose of linezolid or intravenous methylene blue, whichever comes first. Therapy with clomipramine hydrochloride capsules may be resumed 24 hours after the last dose of linezolid or intravenous methylene blue (see WARNINGS).

The risk of administering methylene blue by non-intravenous routes (such as oral tablets or by local injection) or in intravenous doses much lower than 1 mg/kg with clomipramine hydrochloride capsules is unclear. The clinician should, nevertheless, be aware of the possibility of emergent symptoms of serotonin syndrome with such use (see WARNINGS).

HOW SUPPLIED

Clomipramine Hydrochloride Capsules USP

Capsules 25 mg – ivory body imprinted in black with “” and melon-yellow cap imprinted in black with “25 mg”

Bottles of 100................................... NDC 0406-8806-01

Capsules 50 mg – ivory body imprinted in black with “” and aqua blue cap imprinted in black with “50 mg”

Bottles of 100................................... NDC 0406-8807-01

Capsules 75 mg – ivory body imprinted in black with “” and yellow cap imprinted in black with “75 mg”

Bottles of 100................................... NDC 0406-8808-01

Storage – Store at 20° to 25°C (68° to 77°F) [see USP Controlled Room Temperature].

Dispense in well-closed containers with a child-resistant closure. Protect from moisture.

ANIMAL TOXICOLOGY

Phospholipidosis and testicular changes, commonly associated with tricyclic compounds, have been observed with clomipramine hydrochloride capsules. In chronic rat studies, changes related to clomipramine hydrochloride capsules consisted of systemic phospholipidosis, alterations in the testes (atrophy, mineralization) and secondary changes in other tissues. In addition cardiac thrombosis and dermatitis/keratitis were observed in rats treated for 2 years at doses which were
24 and 10 times the maximum recommended human daily dose (MRHD), respectively, on a mg/kg basis, and 4 and 1.5 times the MRHD, respectively, on a mg/m^2 basis.

Mallinckrodt, the “M” brand mark, the Mallinckrodt Pharmaceuticals logo and M are trademarks of a Mallinckrodt company.

© 2024 Mallinckrodt.

Product of Canada, Active Ingredient made in Ireland

Manufactured by

Patheon Inc.

Whitby, Ontario, Canada

L1N 5Z5

for SpecGx LLC

Webster Groves, MO 63119 USA

Rev 09/2024

Mallinckrodt™

Medication Guide Clomipramine Hydrochloride Capsules USP

Antidepressant Medicines, Depression and Other Serious Mental Illnesses,
and Suicidal Thoughts or Actions

Read the Medication Guide that comes with you or your family member’s antidepressant medicine. This Medication Guide is only about the risk of suicidal thoughts and actions with antidepressant medicines. Talk to your, or your family member’s, healthcare provider about:

- all risks and benefits of treatment with antidepressant medicines
- all treatment choices for depression or other serious mental illness

What is the most important information I should know about antidepressant medicines, depression and other serious mental illnesses, and suicidal thoughts or actions?

1. Antidepressant medicines may increase suicidal thoughts or actions in some children, teenagers, and young adults within the first few months of treatment.
2. Depression and other serious mental illnesses are the most important causes of suicidal thoughts and actions. Some people may have a particularly high risk of having suicidal thoughts or actions. These include people who have (or have a family history of) bipolar illness (also called manic-depressive illness) or suicidal thoughts or actions.
3. How can I watch for and try to prevent suicidal thoughts and actions in myself or a family member?

- Pay close attention to any changes, especially sudden changes, in mood, behaviors, thoughts, or feelings. This is very important when an antidepressant medicine is started or when the dose is changed.
- Call the healthcare provider right away to report new or sudden changes in mood, behavior, thoughts, or feelings.
- Keep all follow-up visits with the healthcare provider as scheduled. Call the healthcare provider between visits as needed, especially if you have concerns about symptoms.

Call a healthcare provider right away if you or your family member has any of the following symptoms, especially if they are new, worse, or worry you:

- thoughts about suicide or dying
- attempts to commit suicide
- new or worse depression
- new or worse anxiety
- feeling very agitated or restless
- panic attacks
- trouble sleeping (insomnia)
- new or worse irritability
- acting aggressive, being angry, or violent
- acting on dangerous impulses
- an extreme increase in activity and talking (mania)
- other unusual changes in behavior or mood

Low salt (sodium) levels in the blood. Elderly people may be at greater risk for this. Symptoms may include:

- headache
- weakness or feeling unsteady
- confusion, problems concentrating or thinking or memory problems

Visual problems

- eye pain
- changes in vision
- swelling or redness in or around the eye

Only some people are at risk for these problems. You may want to undergo an eye examination to see if you are at risk and receive preventative treatment if you are.

Who should not take clomipramine hydrochloride capsules?

Do not take clomipramine hydrochloride capsules if you:

- take a monoamine oxidase inhibitor (MAOI). Ask your healthcare provider or pharmacist if you are not sure if you take an MAOI, including the antibiotic linezolid.
  - Do not take an MAOI within 2 weeks of stopping clomipramine hydrochloride capsules unless directed to do so by your physician.
  - Do not start clomipramine hydrochloride capsules if you stopped taking an MAOI in the last 2 weeks unless directed to do so by your physician.

What else do I need to know about antidepressant medicines?

- Never stop an antidepressant medicine without first talking to a healthcare provider. Stopping an antidepressant medicine suddenly can cause other symptoms.
- Antidepressants are medicines used to treat depression and other illnesses. It is important to discuss all the risks of treating depression and also the risks of not treating it. Patients and their families or other caregivers should discuss all treatment choices with the healthcare provider, not just the use of antidepressants.
- Antidepressant medicines have other side effects. Talk to the healthcare provider about the side effects of the medicine prescribed for you or your family member.
- Antidepressant medicines can interact with other medicines. Know all of the medicines that you or your family member takes. Keep a list of all medicines to show the healthcare provider. Do not start new medicines without first checking with your healthcare provider.
- Not all antidepressant medicines prescribed for children are FDA approved for use in children. Talk to your child’s healthcare provider for more information.

Call your doctor for medical advice about side effects. You may report side effects to FDA at 1-800-FDA-1088.

This Medication Guide has been approved by the U.S. Food and Drug Administration.

Product of Canada, Active Ingredient made in Ireland

Manufactured by
Patheon Inc.
Whitby, Ontario, Canada
L1N 5Z5
for SpecGx LLC
Webster Groves, MO 63119 USA

Rev 09/2024

Mallinckrodt™

PACKAGE LABEL - PRINCIPAL DISPLAY PANEL - 25 mg Bottle

NDC 0406-8806-01

100 Capsules

ClomiPRAMINE
Hydrochloride
Capsules USP

25 mg

Each capsule contains:
Clomipramine Hydrochloride USP... 25 mg

PHARMACIST: PLEASE DISPENSE
WITH ATTACHED MEDICATION GUIDE

RX only

Mallinckrodt™

2000017737

Rev 09/2024

PACKAGE LABEL - PRINCIPAL DISPLAY PANEL - 50 mg Bottle

NDC 0406-8807-01

100 Capsules

ClomiPRAMINE
Hydrochloride
Capsules USP

50 mg

Each capsule contains:
Clomipramine Hydrochloride USP... 50 mg

PHARMACIST: PLEASE DISPENSE
WITH ATTACHED MEDICATION GUIDE

RX only

Mallinckrodt™

2000017738

Rev 09/2024

PACKAGE LABEL - PRINCIPAL DISPLAY PANEL - 75 mg Bottle

NDC 0406-8808-01

100 Capsules

ClomiPRAMINE

Hydrochloride

Capsules USP

75 mg

Each capsule contains:

Clomipramine Hydrochloride USP... 75 mg

PHARMACIST: PLEASE DISPENSE

WITH ATTACHED MEDICATION GUIDE

RX only

Mallinckrodt™

2000017739

Rev 09/2024